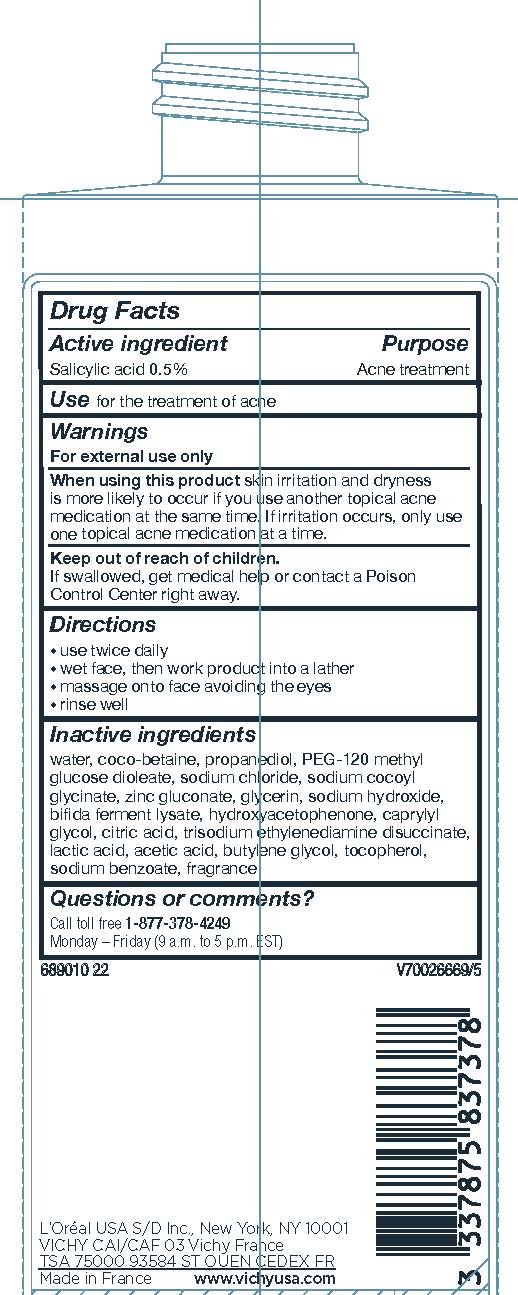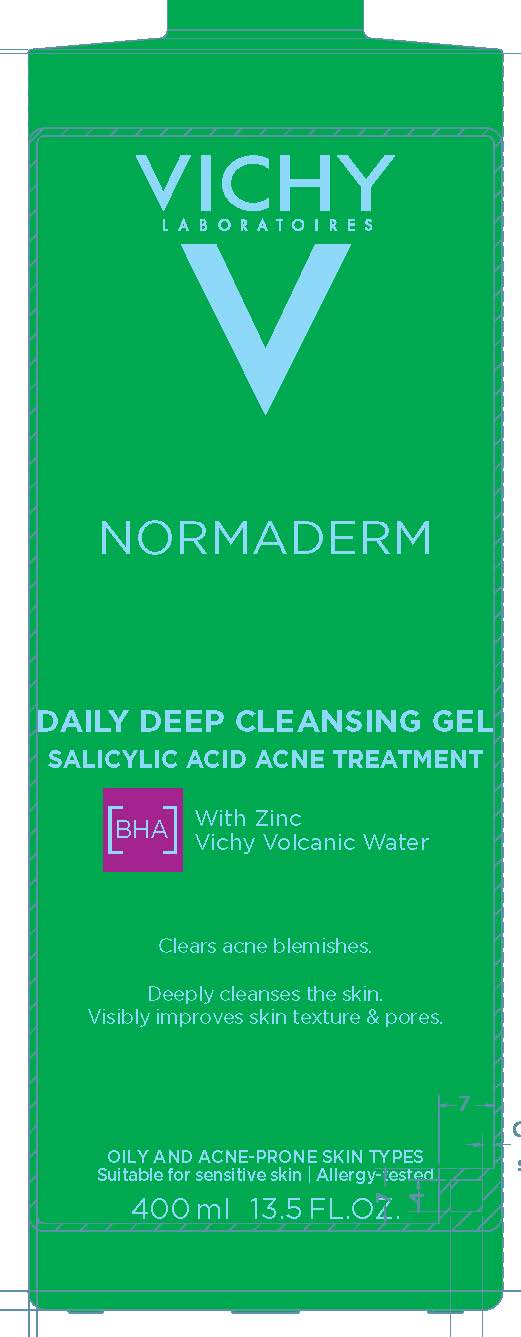 DRUG LABEL: Vichy Laboratoires Normaderm Daily Deep Cleansing  Acne Treatment
NDC: 69625-630 | Form: GEL
Manufacturer: COSMETIQUE ACTIVE PRODUCTION
Category: otc | Type: HUMAN OTC DRUG LABEL
Date: 20240714

ACTIVE INGREDIENTS: Salicylic Acid 5 mg/1 mL
INACTIVE INGREDIENTS: WATER; COCO-BETAINE; PROPANEDIOL; PEG-120 METHYL GLUCOSE DIOLEATE; SODIUM CHLORIDE; SODIUM COCOYL GLYCINATE; ZINC GLUCONATE; GLYCERIN; SODIUM HYDROXIDE; HYDROXYACETOPHENONE; CAPRYLYL GLYCOL; CITRIC ACID MONOHYDRATE; TRISODIUM ETHYLENEDIAMINE DISUCCINATE; LACTIC ACID; ACETIC ACID; BUTYLENE GLYCOL; TOCOPHEROL; SODIUM BENZOATE

Drug Facts

Active ingredient

Salicylic acid...0.05%

Purpose

Acne treatment

Uses

- for the treatment of acne

Warnings

For external use only

When using this product

skin irritation and dryness is more likely to occur if you use another topical acne medication at the same time. if irritation occurs, only use one topical acne medication at a time.

Keep out of reach of children.

If swallowed, get medical help or contact a Poison Control Center right away.

Directions

• use twice daily
• wet face, then work product into a lather
• massage onto face, avoiding eyes
• rinse well

Inactive ingredients

water, coco-betaine, propanediol, PEG-120 methyl glucose dioleate, sodium chloride, sodium cocoyl glycinate, zinc gluconate, glycerin, sodium hydroxide, bifida ferment lysate, hydroxyacetophenone, caprylyl glycol, citric acid, trisodium ethylenediamine disuccinate, lactic acid, acetic acid, butylene glycol. Tocopherol, sodium benzoate, fragrance

Questions or comments?

Call toll free 1-877-378-4249

Monday - Friday (9 a.m. to 5 p.m. EST)